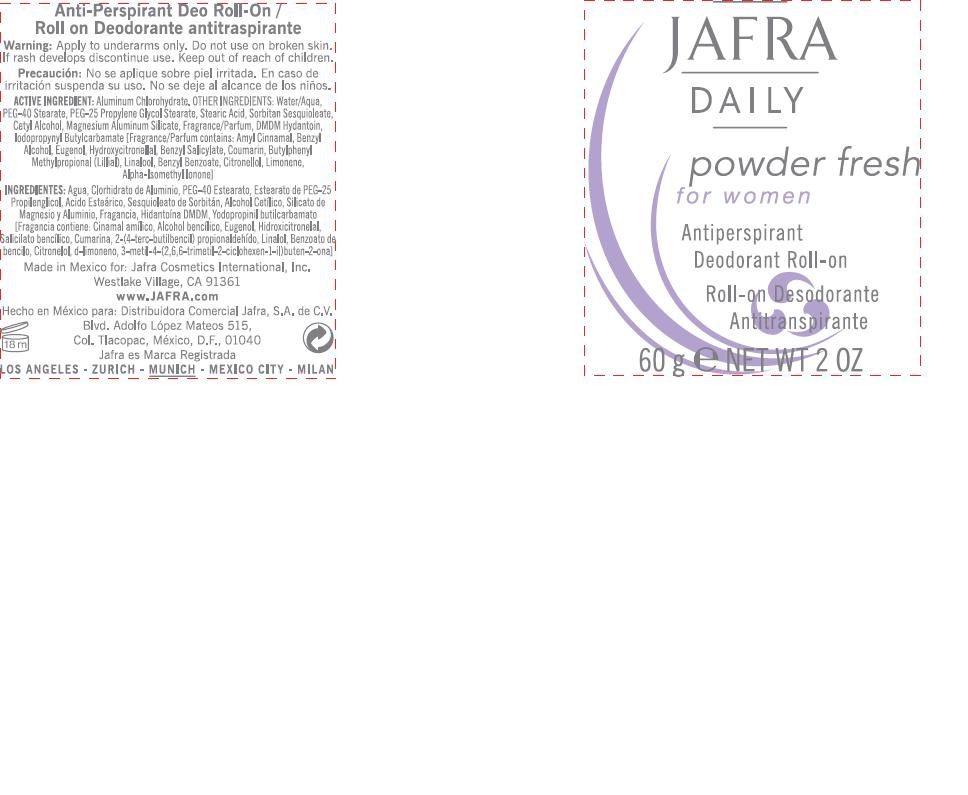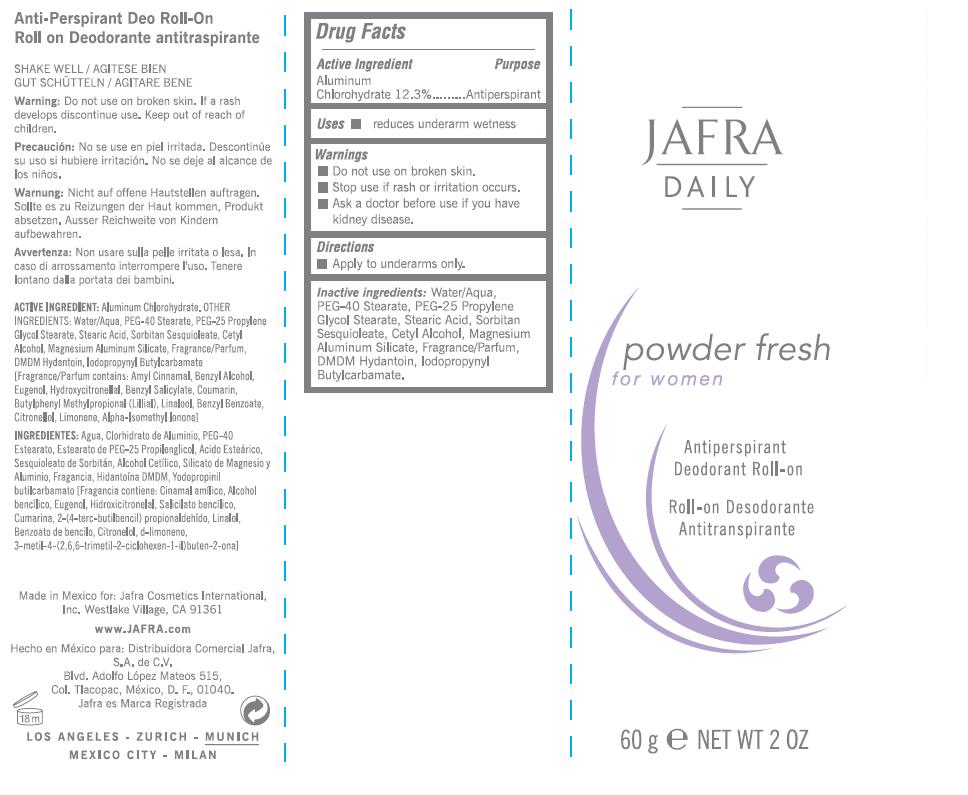 DRUG LABEL: JAFRA DAILY
NDC: 68828-053 | Form: LOTION
Manufacturer: JAFRA COSMETICS INTERNATIONAL
Category: otc | Type: HUMAN OTC DRUG LABEL
Date: 20120501

ACTIVE INGREDIENTS: ALUMINUM CHLOROHYDRATE 12.3 g/100 g
INACTIVE INGREDIENTS: WATER; PEG-40 STEARATE; PEG-25 PROPYLENE GLYCOL STEARATE; STEARIC ACID; SORBITAN SESQUIOLEATE; CETYL ALCOHOL; DMDM HYDANTOIN; MAGNESIUM ALUMINUM SILICATE; IODOPROPYNYL BUTYLCARBAMATE

JAFRA DAILY POWDER FRESH

ACTIVE INGREDIENT:
ALUMINUM CHLOROHYDRATE 12.3%

PURPOSE

ANTIPERSPIRANT

INACTIVE INGREDIENT

INACTIVE INGREDIENTS: WATER/AQUA, PEG-40 STEARATE, PEG-25 PROPYLENE GLYCOL STEARATE, STEARIC ACID, SORBITAN SESQUIOLEATE, CETYL ALCOHOL, MAGNESIUM ALUMINUM SILICATE, FRAGRANCE/PARFUM, DMDM HYDANTOIN, IODOPROPYNYL BUTYLCARBAMATE.

USES

- REDUCES UNDERARM WETNESS

DIRECTIONS

- APPLY TO UNDERARMS ONLY

WARNINGS

- DO NOT USE ON BROKEN SKIN.

- STOP USE IF RASH OR IRRITATION OCCURS.

KEEP OUT OF REACH OF CHILDREN.

PACKAGE LABEL

JAFRA

DAILY
POWDER FRESH
FOR WOMEN
ANTIPERSPIRANT
DEODORANT ROLL-ON
60 G / NET WT 2 OZ

- ASK A DOCTOR BEFORE USE IF YOU HAVE KIDNEY DISEASE.